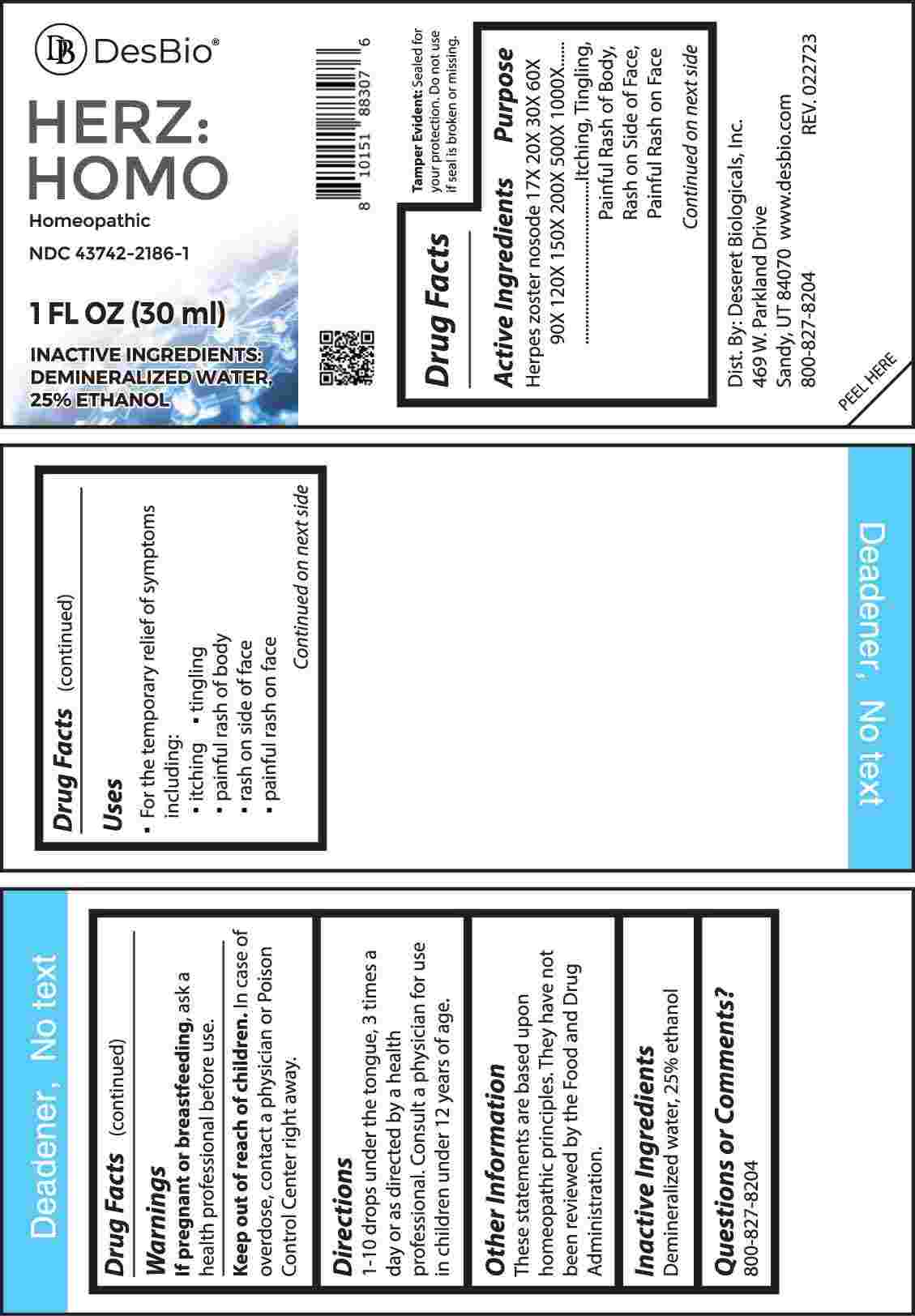 DRUG LABEL: Herz Homo
NDC: 43742-2186 | Form: LIQUID
Manufacturer: Deseret Biologicals, Inc.
Category: homeopathic | Type: HUMAN OTC DRUG LABEL
Date: 20240515

ACTIVE INGREDIENTS: HUMAN HERPESVIRUS 3 17 [hp_X]/1 mL
INACTIVE INGREDIENTS: WATER; ALCOHOL

DRUG FACTS:

ACTIVE INGREDIENTS:

Herpes Zoster Nosode 17X, 20X, 30X, 60X, 90X, 120X, 150X, 200X, 500X, 1000X.

PURPOSE:

Herpes Zoster Nosode - Itching, Tingling, Painful Rash of Body, Rash on Side of Face, Painful Rash on Face

USES:

• For the temporary relief of symptoms including:

• itching • tingling • painful rash of body

• rash on side of face • painful rash on face

These statements are based upon homeopathic principles. They have not been reviewed by the Food and Drug Administration.

WARNINGS:

If pregnant or breast-feeding, ask a health professional before use.

Keep out of reach of children. In case of overdose, contact a physician or Poison Control Center right away.

Tamper Evident: Sealed for your protection. Do not use if seal is broken or missing.

KEEP OUT OF REACH OF CHILDREN:

In case of overdose, contact a physician or Poison Control Center right away.

DIRECTIONS:

1-10 drops under the tongue, 3 times a day or as directed by a health professional. Consult a physician for use in children under 12 years of age.

INACTIVE INGREDIENTS:

Demineralized water, 25% ethanol

QUESTIONS:

Dist. By: Deseret Biologicals, Inc.

469 W. Parkland Drive

Sandy, UT 84070

www.desbio.com

800-827-8204

PACKAGE LABEL DISPLAY:

DesBio

HERZ:HOMO

Homeopathic

NDC 43742-2186-1

1 FL OZ (30 ml)